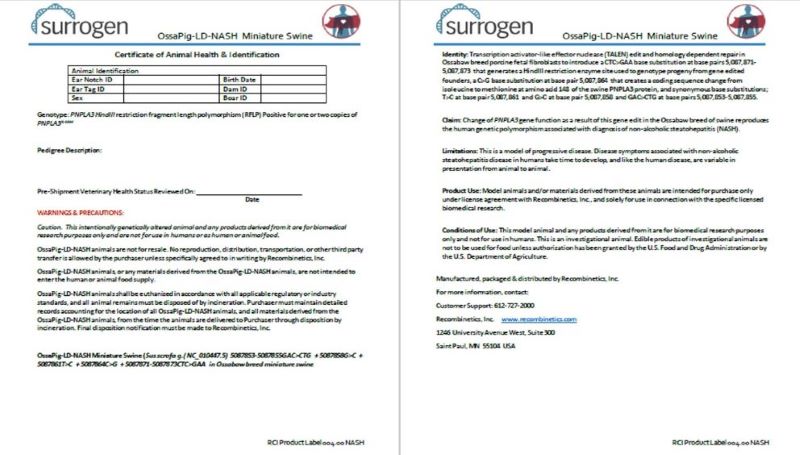 DRUG LABEL: OssaPig-LD-NASH Miniature Swine
NDC: 86086-004 | Form: NOT APPLICABLE
Manufacturer: Recobimbinetics, Inc.
Category: other | Type: INTENTIONAL ANIMAL GENOMIC ALTERATION LABEL
Date: 20240724

ACTIVE INGREDIENTS: SUS SCROFA G.(NC_010447.5) 5087853-5087855GAC>CTG+5087858G>C+5087861T>C+5087864C>G+5087871-5087873CTC>GAA ALTERATION TO EXON 3 OF PNPLA3 GENE IN OSSABAW BREED MINIATURE SWINE 1 [arb'U]/1 [arb'U]

OssaPig-LD-NASH Miniature Swine

STATEMENT OF IDENTITY

Identity: Transcription activator-like effector nuclease (TALEN) edit and homology dependent repair in Ossabaw breed porcine fetal fibroblasts to introduce a CTC>GAA base substitution at base pairs 5,087,871-5,087,873 that generates a HindIII restriction enzyme site used to genotype progeny from gene edited founders, a C>G base substitution at base pair 5,087,864 that creates a coding sequence change from isoleucine to methionine at amino acid 148 of the swine PNPLA3 protein, and synonymous base substitutions; T>C at base pair 5,087,861 and G>C at base pair 5,087,858 and GAC>CTG at base pairs 5,087,853-5,087,855.

HEALTH CLAIM

Claim: Change of PNPLA3 gene function as a result of this gene edit in the Ossabaw breed of swine reproduces the human genetic polymorphism associated with diagnosis of non-alcoholic steatohepatitis (NASH).

CONTRAINDICATIONS

Limitations: This is a model of progressive disease. Disease symptoms associated with non-alcoholic steatohepatitis disease in humans take time to develop, and like the human disease, are variable in presentation from animal to animal.

INDICATIONS AND USAGE

Product Use: Model animals and/or materials derived from these animals are intended for purchase only under license agreement with Recombinetics, Inc., and solely for use in connection with the specific licensed biomedical research.

INDICATIONS AND USAGE

Conditions of Use: This model animal and any products derived from it are for biomedical research purposes only and not for use in humans. This is an investigational animal. Edible products of investigational animals are not to be used for food unless authorization has been granted by the U.S. Food and Drug Administration or by the U.S. Department of Agriculture.

WARNINGS AND PRECAUTIONS

Caution. This intentionally genetically altered animal and any products derived from it are for biomedical research purposes only and are not for use in humans or as human or animal food.
OssaPig-LD-NASH animals are not for resale. No reproduction, distribution, transportation, or other third party transfer is allowed by the purchaser unless specifically agreed to in writing by Recombinetics, Inc.
OssaPig-LD-NASH animals, or any materials derived from the OssaPig-LD-NASH animals, are not intended to enter the human or animal food supply.
OssaPig-LD-NASH animals shall be euthanized in accordance with all applicable regulatory or industry standards, and all animal remains must be disposed of by incineration. Purchaser must maintain detailed records accounting for the location of all OssaPig-LD-NASH animals, and all materials derived from the OssaPig-LD-NASH animals, from the time the animals are delivered to Purchaser through disposition by incineration. Final disposition notification must be made to Recombinetics, Inc.